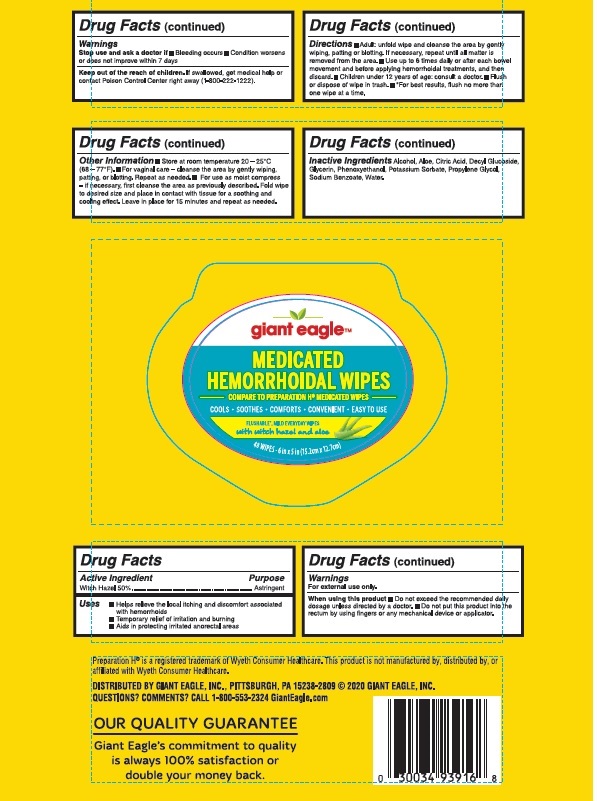 DRUG LABEL: Witch Hazel
NDC: 56194-550 | Form: CLOTH
Manufacturer: Giant Eagle
Category: otc | Type: HUMAN OTC DRUG LABEL
Date: 20251205

ACTIVE INGREDIENTS: WITCH HAZEL 50 g/100 1
INACTIVE INGREDIENTS: POTASSIUM SORBATE; WATER; CITRIC ACID MONOHYDRATE; GLYCERIN; SODIUM BENZOATE; PROPYLENE GLYCOL; PHENOXYETHANOL; ALOE; ALCOHOL; DECYL GLUCOSIDE

Medicated Hemorrhoidal Wipes

Active Ingredient

Witch Hazel 50%

Purpose

Astringent

Uses

- Helps relieve the local itching and discomfort associated with hemorrhoids
- Temporary relief of irritation and burning
- Aids in protecting irritated anorectal areas

Warnings

For external use only.

When using this product

- Do not exceed the recommendeed daily dosage unless directed by a doctor.
- Do not put this product into the rectum by using fingers or any mechanical device or applicator.

Stop use and ask a doctor if

- Bleeding occurs
- Condition worsens or does not improve within 7 days

Keep out of the reach of children.

If swallowed, get medical help or contact Poison Control Center right away (1-800-222-1222).

Directions

- Adult: unfold wipe and cleanse the area by gently wiping, patting or blotting. If necessary, repeat until all matter is removed from the area.
- Use up to 6 times daily or after each bowel movement and before applying hemorrhoidal treatments, and then discard.
- Children under 12 years of age: consult a doctor.
- Flush or dispose of wipe in trash.
- *For best results, flush no more than one wipe at a time.

Other information

- Store at room temperature 20 - 25°C (68 - 77°F).
- For vaginal care - cleanse the area by gently wiping, patting, or blotting. Repeat as needed.
- For use as moist compress - if necessary, first cleanse the area as previously described. Fold wipe to desired size and place in contact with tissue for a soothing and cooling effect. Leave in place for 15 minutes and repeat as needed.

Inactive Ingredients

Alcohol, Aloe, Citric Acid, Decyl Glucoside, Glycerin, Phenoxyethanol, Potassium Sorbate, Propylene Glycol, Sodium Benzoate, Water.

Principal Display Panel

giant eagle

MEDICATED

HEMORRHOIDAL WIPES

COMPARE TO PREPARATION H MEDICATED WIPES

COOLS • SOOTHES • COMFORTS • CONVENIENT • EASY TO USE

FLUSHABLE MILD EVERYDAY WIPES with witch hazel and aloe

48 WIPES • 6 in x 5 in (15.2cm x 12.7cm)